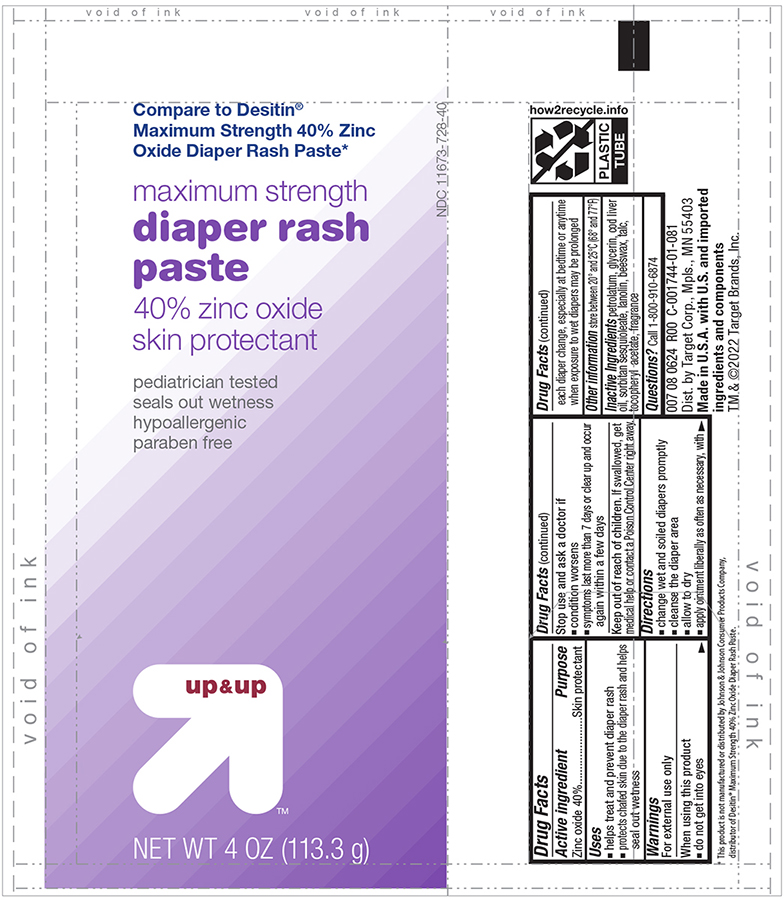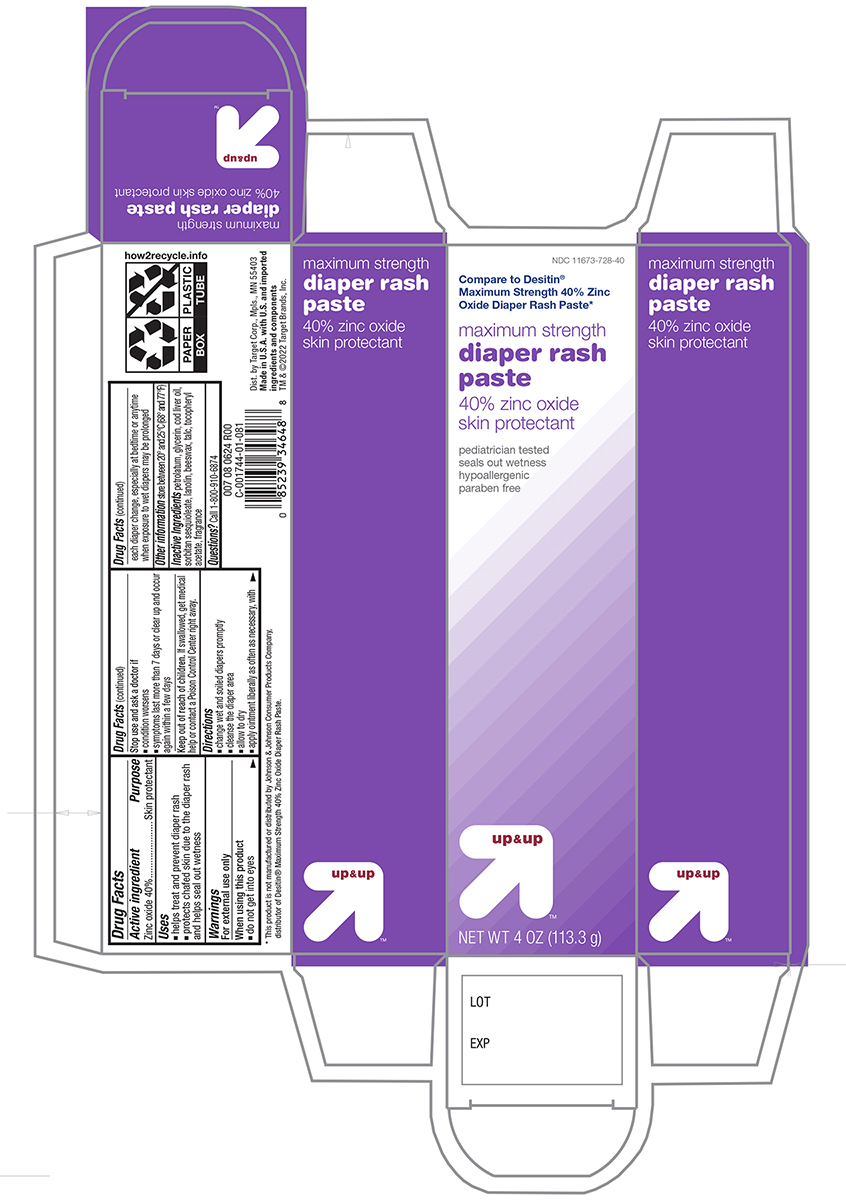 DRUG LABEL: Target Maximum Strength Zinc Oxide Diaper Rash
NDC: 11673-728 | Form: PASTE
Manufacturer: Target Corporation
Category: otc | Type: HUMAN OTC DRUG LABEL
Date: 20241121

ACTIVE INGREDIENTS: ZINC OXIDE 400 mg/1 g
INACTIVE INGREDIENTS: PETROLATUM; GLYCERIN; COD LIVER OIL; SORBITAN SESQUIOLEATE; LANOLIN; YELLOW WAX; TALC; .ALPHA.-TOCOPHEROL ACETATE

Active ingredient

Zinc Oxide 40%

Purpose

Skin protectant

Uses

- helps treat and prevent diaper rash
- protects chafed skin due to diaper rash and helps seal out wetness

Warnings

For external use only

When using this product

- avoid contact with eyes

Stop use and ask a doctor if

- if condition worsens or does not improve in 7 days. This may be a sign of a serious condition.

Keep out of the reach of children

If swallowed, get medical help or contact a Poison Control Center right away.

Directions

- change wet and soiled diapers promptly
- cleanse the diaper area, and allow to dry
- apply ointment liberally as often as necessary, with each diaper change, especially at bedtime or anytime when exposure to wet diapers may be prolonged

Other information

store between 20 and 25 C (68 and 77 F)

Inactive ingredients

Petrolatum, Glycerin, Cod Liver Oil, Sorbitan Sesquioleate, Lanolin, Beeswax, Talc, Tocopheryl Acetate, Fragrance

Principal Display Panel -Tube

Target Up and Up NDC 11673-728-40

Maximum Strength diaper rash Paste

Zino Oxide 40%

Skin Protectant

NET WT 4.0 OZ (113.3g)

Principal Display Panel Carton

Target Up and Up NDC 11673-728-40

Maximum Strength diaper rash Paste

Zino Oxide 40%

Skin Protectant

NET WT 4.0 OZ (113.3g)